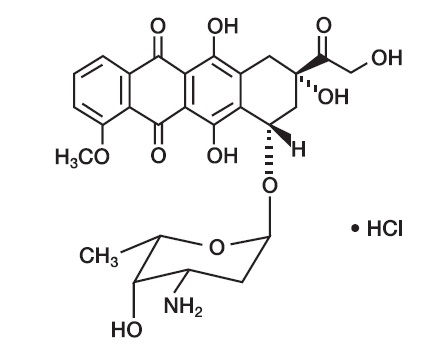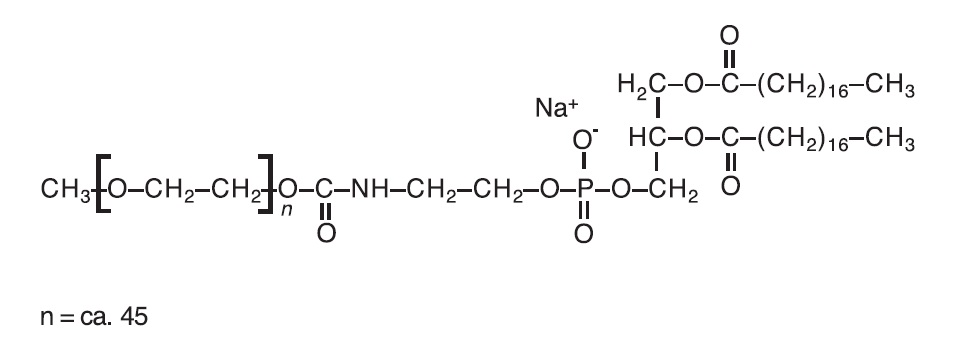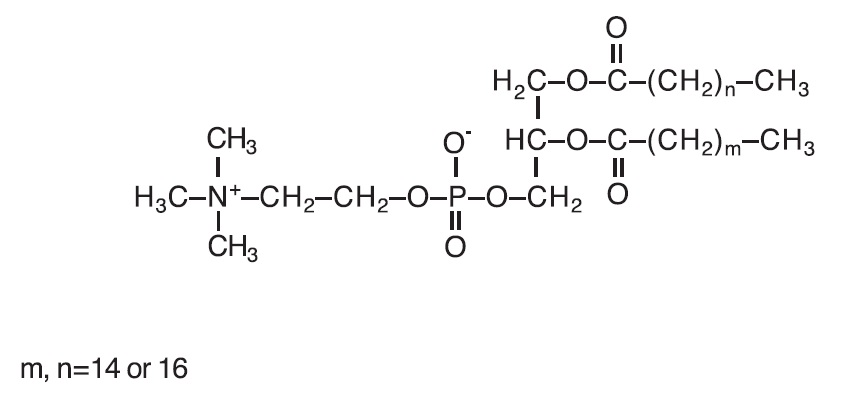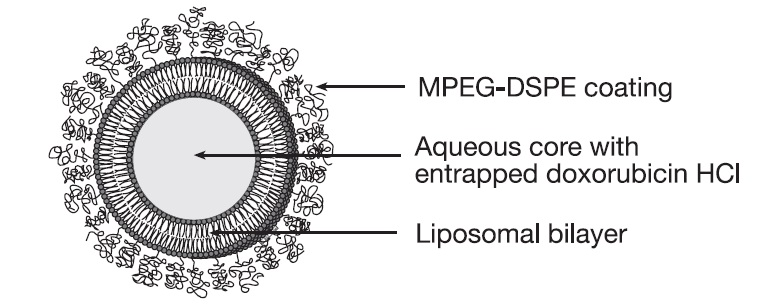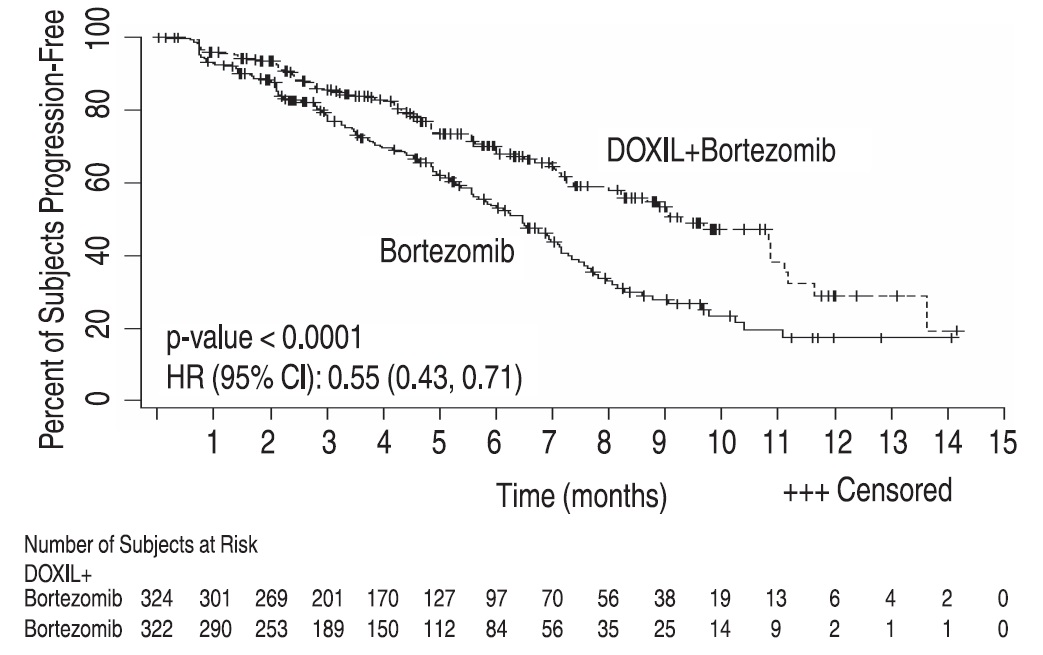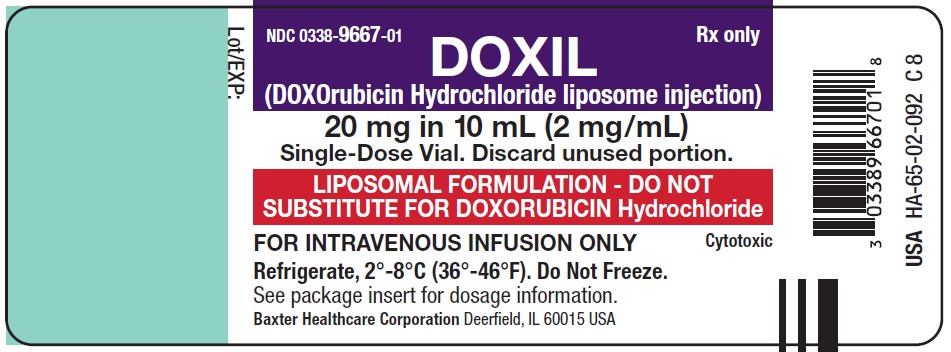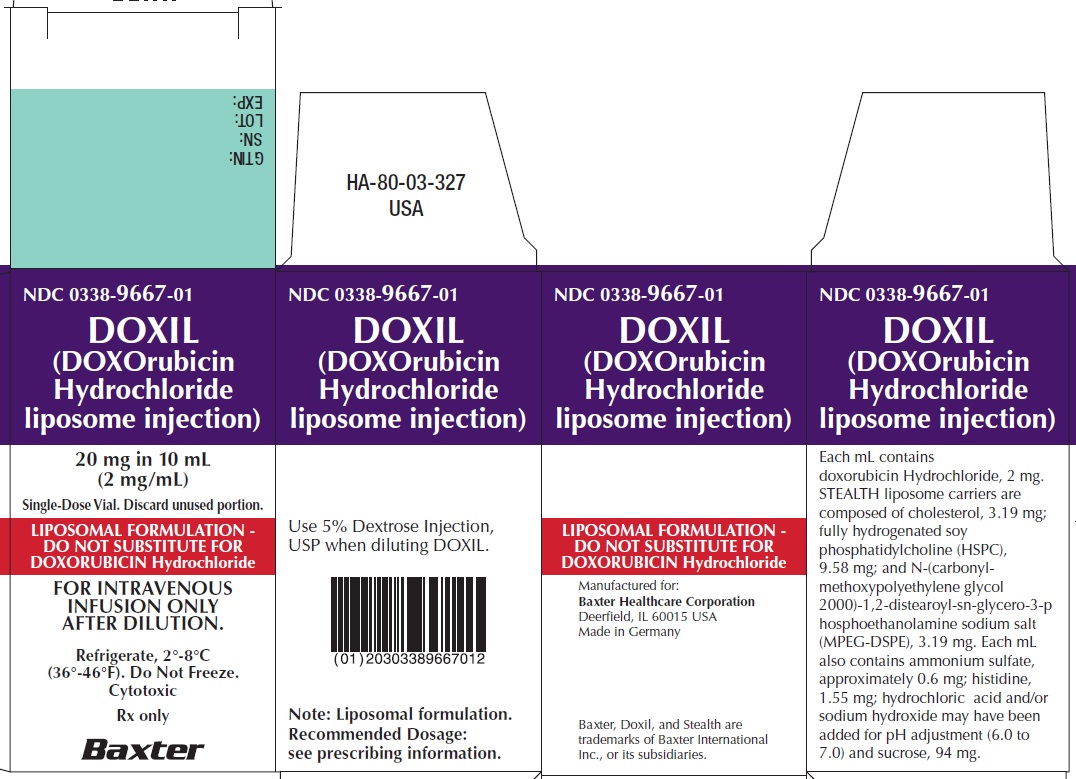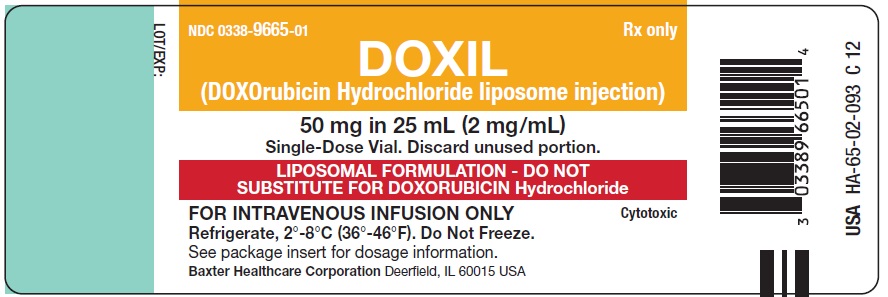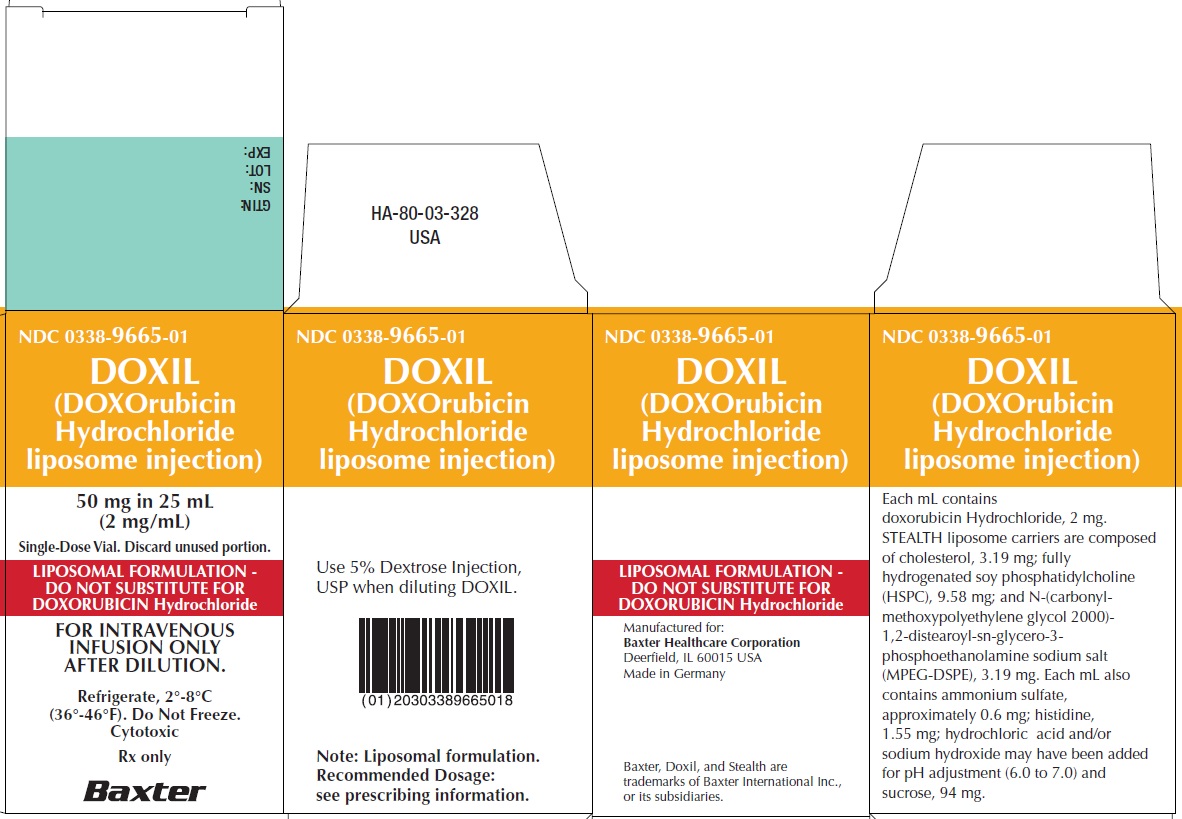 DRUG LABEL: DOXIL
NDC: 0338-9667 | Form: INJECTION, SUSPENSION, LIPOSOMAL
Manufacturer: Baxter Healthcare Corporation
Category: prescription | Type: HUMAN PRESCRIPTION DRUG LABEL
Date: 20260122

ACTIVE INGREDIENTS: doxorubicin hydrochloride 2 mg/1 mL
INACTIVE INGREDIENTS: SODIUM N-(CARBONYL-METHOXYPOLYETHYLENE GLYCOL 2000)-1,2-DISTEAROYL-SN-GLYCERO-3-PHOSPHOETHANOLAMINE 3.19 mg/1 mL; hydrogenated soybean lecithin 9.58 mg/1 mL; cholesterol 3.19 mg/1 mL; ammonium sulfate 0.6 mg/1 mL; histidine 1.55 mg/1 mL; hydrochloric acid; sodium hydroxide; sucrose 94 mg/1 mL

HIGHLIGHTS OF PRESCRIBING INFORMATION

These highlights do not include all the information needed to use DOXIL safely and effectively. See full prescribing information for DOXIL.
DOXIL (doxorubicin hydrochloride liposome injection), for intravenous use
Initial U.S. Approval: 1995

WARNING: CARDIOMYOPATHY and INFUSION-RELATED REACTIONS

See full prescribing information for complete boxed warning.

- DOXIL liposomal infusion can cause myocardial damage, including acute left ventricular failure. The risk of cardiomyopathy was 11% when the cumulative anthracycline dose was between 450 mg/m^2 to 550 mg/m^2. Assess left ventricular cardiac function prior to initiation of DOXIL liposomal infusion, during treatment, and after treatment (5.1).
- Serious, life-threatening, and fatal infusion‑related reactions can occur. Acute infusion-related reactions occurred in 11% of patients with solid tumors. Withhold DOXIL liposomal infusion for infusion-related reactions and resume at a reduced rate. Discontinue DOXIL liposomal infusion for serious or life-threatening infusion-related reactions (5.2).

1 INDICATIONS AND USAGE

DOXIL liposomal infusion is an anthracycline topoisomerase inhibitor indicated for:

- Ovarian cancer: After failure of platinum-based chemotherapy (1.1)
- AIDS-related Kaposi’s Sarcoma: After failure of prior systemic chemotherapy or intolerance to such therapy (1.2)
- Multiple Myeloma: In combination with bortezomib in patients who have not previously received bortezomib and have received at least one prior therapy (1.3)

2 DOSAGE AND ADMINISTRATION

Administer DOXIL liposomal infusion at an initial rate of 1 mg/min to minimize the risk of infusion reactions. If no infusion-related reactions occur, increase rate of infusion to complete administration over 1 hour. Do not administer as bolus injection or undiluted solution (2).

- Ovarian cancer: 50 mg/m^2 intravenously every 4 weeks (2.2)
- AIDS-related Kaposi’s Sarcoma: 20 mg/m^2 intravenously every 3 weeks (2.3)
- Multiple Myeloma: 30 mg/m^2 intravenously on day 4 following bortezomib (2.4)

3 DOSAGE FORMS AND STRENGTHS

Doxorubicin hydrochloride liposomal injection: 20 mg/10 mL (2 mg/mL) and 50 mg/25 mL (2 mg/mL) in single dose vials (3)

4 CONTRAINDICATIONS

- Hypersensitivity reactions to doxorubicin hydrochloride or the components of DOXIL liposomal infusion (4, 5.2)

5 WARNINGS AND PRECAUTIONS

- Hand-Foot Syndrome may occur. Dose modification or discontinuation may be required (5.3)
- Embryo-Fetal Toxicity: Can cause fetal harm. Advise of potential risk to a fetus. Use effective contraception (5.5, 8.1, 8.3)

6 ADVERSE REACTIONS

Most common adverse reactions (>20%) are asthenia, fatigue, fever, anorexia, nausea, vomiting, stomatitis, diarrhea, constipation, hand-foot syndrome, rash, neutropenia, thrombocytopenia, and anemia (6).

To report SUSPECTED ADVERSE REACTIONS contact Baxter Healthcare at 1-866-888-2472 or FDA at 1-800-FDA-1088 or www.fda.gov/medwatch.

8 USE IN SPECIFIC POPULATIONS

- Lactation: Discontinue breastfeeding (8.2).

FULL PRESCRIBING INFORMATION

WARNING: CARDIOMYOPATHY and INFUSION-RELATED REACTIONS

- DOXIL liposomal infusion can cause myocardial damage, including acute left ventricular failure. The risk of cardiomyopathy was 11% when the cumulative anthracycline dose was between 450 mg/m^2 to 550 mg/m^2. Assess left ventricular cardiac function prior to initiation of DOXIL liposomal infusion and during and after treatment [see Warnings and Precautions (5.1)].
- Serious, life-threatening, and fatal infusion-related reactions can occur with DOXIL liposomal infusion Acute infusion-related reactions occurred in 11% of patients with solid tumors. Withhold DOXIL liposomal infusion for infusion-related reactions and resume at a reduced rate. Discontinue DOXIL liposomal infusion for serious or life-threatening infusion-related reactions [see Warnings and Precautions (5.2)].

1 INDICATIONS AND USAGE

1.1 Ovarian Cancer

DOXIL liposomal infusion is indicated for the treatment of patients with ovarian cancer whose disease has progressed or recurred after platinum-based chemotherapy.

1.2 AIDS-Related Kaposi’s Sarcoma

DOXIL liposomal infusion is indicated for the treatment of AIDS-related Kaposi's sarcoma in patients after failure of prior systemic chemotherapy or intolerance to such therapy.

1.3 Multiple Myeloma

DOXIL liposomal infusion, in combination with bortezomib, is indicated for the treatment of patients with multiple myeloma who have not previously received bortezomib and have received at least one prior therapy.

2 DOSAGE AND ADMINISTRATION

2.1 Important Use Information

Do not substitute DOXIL liposomal infusion for other doxorubicin hydrochloride products.

Do not administer as an undiluted suspension or as an intravenous bolus [see Warnings and Precautions (5.2)].

2.2 Ovarian Cancer

The recommended dose of DOXIL liposomal infusion is 50 mg/m^2 intravenously over 60 minutes every 28 days until disease progression or unacceptable toxicity.

2.3 AIDS-Related Kaposi’s Sarcoma

The recommended dose of DOXIL liposomal infusion is 20 mg/m^2 intravenously over 60 minutes every 21 days until disease progression or unacceptable toxicity.

2.4 Multiple Myeloma

The recommended dose of DOXIL liposomal infusion is 30 mg/m^2 intravenously over 60 minutes on day 4 of each 21-day cycle for eight cycles or until disease progression or unacceptable toxicity. Administer DOXIL liposomal infusion after bortezomib on day 4 of each cycle [see Clinical Studies (14.3)].

2.5 Dose Modifications for Adverse Reactions

Do not increase DOXIL liposomal infusion after a dose reduction for toxicity.

Table 1: Recommended Dose Modifications for Hand-Foot Syndrome, Stomatitis, or Hematologic Adverse Reactions
Toxicity | Dose Adjustment
Hand-Foot Syndrome (HFS)
Grade 1: Mild erythema, swelling, or desquamation not interfering with daily activities | - If no previous Grade 3 or 4 HFS: no dose adjustment. - If previous Grade 3 or 4 HFS: delay dose up to 2 weeks, then decrease dose by 25%.
Grade 2: Erythema, desquamation, or swelling interfering with, but not precluding normal physical activities; small blisters or ulcerations less than 2 cm in diameter | - Delay dosing up to 2 weeks or until resolved to Grade 0–1. - Discontinue DOXIL liposomal infusion if no resolution after 2 weeks. - If resolved to Grade 0–1 within 2 weeks: - And no previous Grade 3 or 4 HFS: continue treatment at previous dose. - And previous Grade 3 or 4 toxicity: decrease dose by 25%.
Grade 3: Blistering, ulceration, or swelling interfering with walking or normal daily activities; cannot wear regular clothing | - Delay dosing up to 2 weeks or until resolved to Grade 0–1, then decrease dose by 25%. - Discontinue DOXIL liposomal infusion if no resolution after 2 weeks.
Grade 4: Diffuse or local process causing infectious complications, or a bed ridden state or hospitalization | - Delay dosing up to 2 weeks or until resolved to Grade 0–1, then decrease dose by 25%. - Discontinue DOXIL liposomal infusion if no resolution after 2 weeks.
Stomatitis
Grade 1: Painless ulcers, erythema, or mild soreness | - If no previous Grade 3 or 4 toxicity: no dose adjustment. - If previous Grade 3 or 4 toxicity: delay up to 2 weeks then decrease dose by 25%.
Grade 2: Painful erythema, edema, or ulcers, but can eat | - Delay dosing up to 2 weeks or until resolved to Grade 0–1. - Discontinue DOXIL liposomal infusion if there is no resolution after 2 weeks. - If resolved to Grade 0–1 within 2 weeks: - And no previous Grade 3 or 4 stomatitis: resume treatment at previous dose. - And previous Grade 3 or 4 toxicity: decrease dose by 25%.
Grade 3: Painful erythema, edema, or ulcers, and cannot eat | - Delay dosing up to 2 weeks or until resolved to Grade 0–1. Decrease dose by 25% and return to original dose interval. - If after 2 weeks there is no resolution, discontinue DOXIL liposomal infusion.
Grade 4: Requires parenteral or enteral support | - Delay dosing up to 2 weeks or until resolved to Grade 0–1. Decrease dose by 25% and return to original dose interval. - If after 2 weeks there is no resolution, discontinue DOXIL liposomal infusion.
Neutropenia or Thrombocytopenia
Grade 1 | No dose reduction
Grade 2 | Delay until ANC ≥ 1,500 and platelets ≥ 75,000; resume treatment at previous dose
Grade 3 | Delay until ANC ≥ 1,500 and platelets ≥ 75,000; resume treatment at previous dose
Grade 4 | Delay until ANC ≥ 1,500 and platelets ≥ 75,000; resume at 25% dose reduction or continue previous dose with prophylactic granulocyte growth factor

Table 2: Recommended Dose Modifications of DOXIL Liposomal Infusion for Toxicity When Administered in Combination With Bortezomib
Toxicity | DOXIL Liposomal Infusion
Fever ≥38°C and ANC <1,000/mm^3 | - Withhold dose for this cycle if before Day 4; - Decrease dose by 25%, if after Day 4 of previous cycle.
On any day of drug administration after Day 1 of each cycle:; - Platelet count <25,000/mm^3 - Hemoglobin <8 g/dL - ANC <500/mm^3 | - Withhold dose for this cycle if before Day 4; - Decrease dose by 25%, if after Day 4 of previous cycle AND if bortezomib is reduced for hematologic toxicity.
Grade 3 or 4 non-hematologic drug related toxicity | Do not dose until recovered to Grade <2, then reduce dose by 25%.

For neuropathic pain or peripheral neuropathy, no dosage adjustments are required for DOXIL liposomal infusion. Refer to bortezomib manufacturer’s prescribing information.

2.6 Preparation and Administration

Preparation

Dilute DOXIL liposomal infusion doses up to 90 mg in 250 mL of 5% Dextrose Injection, USP prior to administration. Dilute doses exceeding 90 mg in 500 mL of 5% Dextrose Injection, USP prior to administration. Refrigerate diluted DOXIL liposomal infusion at 2°C to 8°C (36°F to 46°F) and administer within 24 hours.

Administration

Inspect parenteral drug products visually for particulate matter and discoloration prior to administration, whenever solution and container permit. Do not use if a precipitate or foreign matter is present.

Do not use with in-line filters.

Administer the first dose of DOXIL liposomal infusion at an initial rate of 1 mg/min. If no infusion-related adverse reactions are observed, increase the infusion rate to complete the administration of the drug over one hour [see Warnings and Precautions (5.2)]. Do not rapidly flush the infusion line.

Do not mix DOXIL liposomal infusion with other drugs.

Management of Suspected Extravasation

Discontinue DOXIL liposomal infusion for burning or stinging sensation or other evidence indicating perivenous infiltration or extravasation. Manage confirmed or suspected extravasation as follows:

- Do not remove the needle until attempts are made to aspirate extravasated fluid
- Do not flush the line
- Avoid applying pressure to the site
- Apply ice to the site intermittently for 15 minute 4 times a day for 3 days
- If the extravasation is in an extremity, elevate the extremity

2.7 Procedure for Proper Handling and Disposal

DOXIL liposomal infusion is a cytotoxic drug. Follow applicable special handling and disposal procedures.^1 If DOXIL liposomal infusion comes into contact with skin or mucosa, immediately wash thoroughly with soap and water.

3 DOSAGE FORMS AND STRENGTHS

DOXIL (doxorubicin hydrochloride liposome injection): 20 mg/10 mL (2 mg/mL) and 50 mg/25 mL (2 mg/mL) translucent, red liposomal dispersion in single dose vials.

4 CONTRAINDICATIONS

DOXIL liposomal infusion is contraindicated in patients who have a history of severe hypersensitivity reactions, including anaphylaxis, to doxorubicin hydrochloride [see Warnings and Precautions (5.2)].

5 WARNINGS AND PRECAUTIONS

5.1 Cardiomyopathy

Doxorubicin hydrochloride can cause myocardial damage, including acute left ventricular failure. The risk of cardiomyopathy with doxorubicin hydrochloride is generally proportional to the cumulative exposure. Include prior use of other anthracyclines or anthracenediones in calculations of cumulative dose. The risk of cardiomyopathy may be increased at lower cumulative doses in patients with prior mediastinal irradiation.

In a clinical study in 250 patients with advanced cancer who were treated with DOXIL liposomal infusion, the risk of cardiomyopathy was 11% when the cumulative anthracycline dose was between 450 mg/m^2 to 550 mg/m^2. Cardiomyopathy was defined as >20% decrease in resting left ventricular ejection fraction (LVEF) from baseline where LVEF remained in the normal range or a >10% decrease in LVEF from baseline where LVEF was less than the institutional lower limit of normal. Two percent of patients developed signs and symptoms of congestive heart failure without documented evidence of cardiomyopathy.

Assess left ventricular cardiac function (e.g. MUGA or echocardiogram) prior to initiation of DOXIL liposomal infusion, during treatment to detect acute changes, and after treatment to detect delayed cardiomyopathy. Administer DOXIL liposomal infusion to patients with a history of cardiovascular disease only when the potential benefit of treatment outweighs the risk.

5.2 Infusion-Related Reactions

Serious, life-threatening, and fatal infusion-related reactions characterized by one or more of the following symptoms can occur with DOXIL liposomal infusion: flushing, shortness of breath, facial swelling, headache, chills, chest pain, back pain, tightness in the chest and throat, fever, tachycardia, pruritus, rash, cyanosis, syncope, bronchospasm, asthma, apnea, and hypotension. Of 239 patients with ovarian cancer treated with DOXIL liposomal infusion in Trial 4, 7% of patients experienced acute infusion-related reactions resulting in dose interruption. All occurred during cycle 1 and none during subsequent cycles. Across multiple studies of DOXIL liposomal infusion monotherapy including this and other studies enrolling 760 patients with various solid tumors, 11% of patients had infusion-related reactions. The majority of infusion-related events occurred during the first infusion.

Ensure that medications to treat infusion-related reactions and cardiopulmonary resuscitative equipment are available for immediate use prior to initiation of DOXIL liposomal infusion. Initiate DOXIL liposomal infusions at a rate of 1 mg/min and increase rate as tolerated [see Dosage and Administration (2.6)]. Withhold DOXIL liposomal infusion for Grade 1, 2, or 3 infusion-related reactions and resume at a reduced infusion rate. Discontinue DOXIL liposomal infusion for serious or life-threatening infusion-related reactions.

5.3 Hand-Foot Syndrome (HFS)

In Trial 4, the incidence of HFS was 51% of patients in the DOXIL liposomal infusion arm and 0.9% of patients in the topotecan arm, including 24% Grade 3 or 4 cases of HFS in DOXIL liposomal infusion-treated patients and no Grade 3 or 4 cases in topotecan-treated patients. HFS or other skin toxicity required discontinuation of DOXIL liposomal infusion in 4.2% of patients.

HFS was generally observed after 2 or 3 cycles of treatment but may occur earlier. Delay DOXIL liposomal infusion for the first episode of Grade 2 or greater HFS [see Dosage and Administration (2.5)]. Discontinue DOXIL liposomal infusion if HFS is severe and debilitating.

5.4 Secondary Oral Neoplasms

Secondary oral cancers, primarily squamous cell carcinoma, have been reported from post-marketing experience in patients with long-term (more than one year) exposure to DOXIL liposomal infusion. These malignancies were diagnosed both during treatment with DOXIL liposomal infusion and up to 6 years after the last dose. Examine patients at regular intervals for the presence of oral ulceration or with any oral discomfort that may be indicative of secondary oral cancer.

The altered pharmacokinetics and preferential tissue distribution of liposomal doxorubicin that contributes to enhanced skin toxicity and mucositis compared to free doxorubicin may play a role in the development of oral secondary malignancies with long-term use.

5.5 EmbryoFetal Toxicity

Based on findings in animals and its mechanism of action, DOXIL liposomal infusion can cause fetal harm when administered to a pregnant woman; avoid the use of DOXIL liposomal infusion during the 1st trimester. Available human data do not establish the presence or absence of major birth defects and miscarriage related to the use of doxorubicin hydrochloride during the 2nd and 3rd trimesters. At doses approximately 0.12 times the recommended clinical dose, DOXIL liposomal infusion was embryotoxic and abortifacient in rabbits. Advise pregnant women of the potential risk to a fetus. Advise females and males of reproductive potential to use effective contraception during and for 6 months after treatment with DOXIL liposomal infusion [see Use in Specific Populations (8.1, 8.3)].

6 ADVERSE REACTIONS

The following adverse reactions are discussed in more detail in other sections of the labeling.

- Cardiomyopathy [see Warnings and Precautions (5.1)]
- Infusion-Related Reactions [see Warnings and Precautions (5.2)]
- Hand-Foot Syndrome [see Warnings and Precautions (5.3)]
- Secondary Oral Neoplasms [see Warnings and Precautions (5.4)]

6.1 Clinical Trials Experience

Because clinical trials are conducted under widely varying conditions, the adverse reaction rates observed cannot be directly compared to rates on other clinical trials and may not reflect the rates observed in clinical practice.

The safety data reflect exposure to DOXIL liposomal infusion in 1310 patients including: 239 patients with ovarian cancer, 753 patients with AIDS-related Kaposi’s sarcoma, and 318 patients with multiple myeloma.

The most common adverse reactions (>20%) observed with DOXIL liposomal infusion are asthenia, fatigue, fever, nausea, stomatitis, vomiting, diarrhea, constipation, anorexia, hand-foot syndrome, rash and neutropenia, thrombocytopenia and anemia.

The following tables present adverse reactions from clinical trials of single-agent DOXIL liposomal infusion in ovarian cancer and AIDS-Related Kaposi’s sarcoma.

Patients With Ovarian Cancer

The safety data described below are from Trial 4, which included 239 patients with ovarian cancer treated with DOXIL liposomal infusion 50 mg/m^2 once every 4 weeks for a minimum of four courses in a randomized, multicenter, open-label study. In this trial, patients received DOXIL liposomal infusion for a median number of 3.2 months (range 1 day to 25.8 months). The median age of the patients is 60 years (range 27 to 87), with 91% Caucasian, 6% Black, and 3% Hispanic or Other.

Table 3 presents the hematologic adverse reactions from Trial 4.

Table 3: Hematologic Adverse Reactions in Trial 4
 | DOXIL Liposomal Infusion Patients (n=239) | Topotecan Patients (n=235)
Neutropenia
500 – <1000/mm^3 | 8% | 14%
<500/mm^3 | 4.2% | 62%
Anemia
6.5 – <8 g/dL | 5% | 25%
< 6.5 g/dL | 0.4% | 4.3%
Thrombocytopenia
10,000 – <50,000/mm^3 | 1.3% | 17%
<10,000/mm^3 | 0.0% | 17%

Table 4 presents the non-hematologic adverse reactions from Trial 4.

Table 4: Non-Hematologic Adverse Reactions in Trial 4
Non-Hematologic Adverse Reaction 10% or Greater | DOXIL Liposomal Infusion (%) treated (n=239) |  | Topotecan (%) treated (n=235)
 | All grades | Grades 3–4 | All grades | Grades 3–4
Body as a Whole
Asthenia | 40 | 7 | 52 | 8
Fever | 21 | 0.8 | 31 | 6
Mucous Membrane Disorder | 14 | 3.8 | 3.4 | 0
Back Pain | 12 | 1.7 | 10 | 0.9
Infection | 12 | 2.1 | 6 | 0.9
Headache | 11 | 0.8 | 15 | 0
Digestive
Nausea | 46 | 5 | 63 | 8
Stomatitis | 41 | 8 | 15 | 0.4
Vomiting | 33 | 8 | 44 | 10
Diarrhea | 21 | 2.5 | 35 | 4.2
Anorexia | 20 | 2.5 | 22 | 1.3
Dyspepsia | 12 | 0.8 | 14 | 0
Nervous
Dizziness | 4.2 | 0 | 10 | 0
Respiratory
Pharyngitis | 16 | 0 | 18 | 0.4
Dyspnea | 15 | 4.1 | 23 | 4.3
Cough increased | 10 | 0 | 12 | 0
Skin and Appendages
Hand-foot syndrome | 51 | 24 | 0.9 | 0
Rash | 29 | 4.2 | 12 | 0.4
Alopecia | 19 | N/A | 52 | N/A

The following additional adverse reactions were observed in patients with ovarian cancer with doses administered every four weeks (Trial 4).

Incidence 1% to 10%

Cardiovascular: vasodilation, tachycardia, deep vein thrombosis, hypotension, cardiac arrest.

Digestive: oral moniliasis, mouth ulceration, esophagitis, dysphagia, rectal bleeding, ileus.

Hematologic and Lymphatic: ecchymosis.

Metabolic and Nutritional: dehydration, weight loss, hyperbilirubinemia, hypokalemia, hypercalcemia, hyponatremia.

Nervous: somnolence, dizziness, depression.

Respiratory: rhinitis, pneumonia, sinusitis, epistaxis.

Skin and Appendages: pruritus, skin discoloration, vesiculobullous rash, maculopapular rash, exfoliative dermatitis, herpes zoster, dry skin, herpes simplex, fungal dermatitis, furunculosis, acne.

Special Senses: conjunctivitis, taste perversion, dry eyes.

Urinary: urinary tract infection, hematuria, vaginal moniliasis.

Patients With AIDS-Related Kaposi’s Sarcoma

The safety data described is based on the experience reported in 753 patients with AIDS-related Kaposi’s sarcoma (KS) enrolled in four open-label, uncontrolled trials of DOXIL liposomal infusion administered at doses ranging from 10 to 40 mg/m^2 every 2 to 3 weeks. Demographics of the population were: median age 38.7 years (range 24–70); 99% male; 88% Caucasian, 6% Hispanic, 4% Black, and 2% Asian/other/unknown. The majority of patients were treated with 20 mg/m^2 of DOXIL liposomal infusion every 2 to 3 weeks with a median exposure of 4.2 months (range 1 day to 26.6 months). The median cumulative dose was 120 mg/m^2 (range 3.3 to 798.6 mg/m^2); 3% received cumulative doses of greater than 450 mg/m^2.

Disease characteristics were: 61% poor risk for KS tumor burden, 91% poor risk for immune system, and 47% poor risk for systemic illness; 36% were poor risk for all three categories; median CD4 count 21 cells/mm^3 (51% less than 50 cells/mm^3); mean absolute neutrophil count at study entry approximately 3,000 cells/mm^3.

Of the 693 patients with concomitant medication information, 59% were on one or more antiretroviral medications [35% zidovudine (AZT), 21% didanosine (ddI), 16% zalcitabine (ddC), and 10% stavudine (D4T)]; 85% received PCP prophylaxis (54% sulfamethoxazole/trimethoprim); 85% received antifungal medications (76% fluconazole); 72% received antivirals (56% acyclovir, 29% ganciclovir, and 16% foscarnet) and 48% patients received colony-stimulating factors (sargramostim/filgrastim) during their course of treatment.

Adverse reactions led to discontinuation of treatment in 5% of patients with AIDS-related Kaposi’s sarcoma and included myelosuppression, cardiac adverse reactions, infusion-related reactions, toxoplasmosis, HFS, pneumonia, cough/dyspnea, fatigue, optic neuritis, progression of a non-KS tumor, allergy to penicillin, and unspecified reasons. Table 5 and Table 6 summarize adverse reactions reported in patients treated with DOXIL liposomal infusion for AIDS-related Kaposi’s sarcoma in a pooled analysis of the four trials.

Table 5: Hematologic Adverse Reactions Reported in Patients With AIDS-Related Kaposi’s Sarcoma
 | Patients With Refractory or Intolerant AIDS-Related Kaposi’s Sarcoma (n=74 [This includes a subset of subjects who were retrospectively identified as having disease progression on prior systemic combination chemotherapy (at least 2 cycles of a regimen containing at least 2 of 3 treatments: bleomycin, vincristine or vinblastine, or doxorubicin) or as being intolerant to such therapy.]) | Total Patients With AIDS-Related Kaposi’s Sarcoma (n=720 [This includes only subjects with AIDS-KS who had available data from the 4 pooled trials.])
Neutropenia
< 1000/mm^3 | 46% | 49%
< 500/mm^3 | 11% | 13%
Anemia
< 10 g/dL | 58% | 55%
< 8 g/dL | 16% | 18%
Thrombocytopenia
< 150,000/mm^3 | 61% | 61%
< 25,000/mm^3 | 1.4% | 4.2%

Table 6: Non-Hematologic Adverse Reactions Reported in ≥ 5% of Patients With AIDS-Related Kaposi’s Sarcoma
Adverse Reactions | Patients With Refractory or Intolerant AIDS-Related Kaposi’s Sarcoma (n=77 [This includes a subset of subjects who were retrospectively identified as having disease progression on prior systemic combination chemotherapy (at least 2 cycles of a regimen containing at least 2 of 3 treatments: bleomycin, vincristine or vinblastine, or doxorubicin) or as being intolerant to such therapy.]) | Total Patients With AIDS-Related Kaposi’s Sarcoma (n=705 [This includes only subjects with AIDS-KS who had available adverse event data from the 4 pooled trials.])
Nausea | 18% | 17%
Asthenia | 7% | 10%
Fever | 8% | 9%
Alopecia | 9% | 9%
Alkaline Phosphatase Increase | 1.3% | 8%
Vomiting | 8% | 8%
Diarrhea | 5% | 8%
Stomatitis | 5% | 7%
Oral Moniliasis | 1.3% | 6%

The following additional adverse reactions were observed in 705 patients with AIDS-related Kaposi’s sarcoma.

Incidence 1% to 5%

Body as a Whole: headache, back pain, infection, allergic reaction, chills.

Cardiovascular: chest pain, hypotension, tachycardia.

Cutaneous: herpes simplex, rash, itching.

Digestive: mouth ulceration, anorexia, dysphagia.

Metabolic and Nutritional: SGPT increase, weight loss, hyperbilirubinemia.

Other: dyspnea, pneumonia, dizziness, somnolence.

Incidence Less Than 1%

Body As A Whole: sepsis, moniliasis, cryptococcosis.

Cardiovascular: thrombophlebitis, cardiomyopathy, palpitation, bundle branch block, congestive heart failure, heart arrest, thrombosis, ventricular arrhythmia.

Digestive: hepatitis.

Metabolic and Nutritional Disorders: dehydration.

Respiratory: cough increase, pharyngitis.

Skin and Appendages: maculopapular rash, herpes zoster.

Special Senses: taste perversion, conjunctivitis.

Patients With Multiple Myeloma

The safety data described are from 318 patients treated with DOXIL liposomal infusion (30 mg/m^2) administered on day 4 following bortezomib (1.3 mg/m^2 i.v. bolus on days 1, 4, 8 and 11) every 3 weeks, in a randomized, open-label, multicenter study (Trial 6). In this trial, patients in the DOXIL liposomal infusion + bortezomib combination group were treated for a median number of 4.5 months (range 21 days to 13.5 months). The population was 28 to 85 years of age (median age 61), 58% male, 90% Caucasian, 6% Black, and 4% Asian and Other. Table 7 lists adverse reactions reported in 10% or more of patients treated with DOXIL liposomal infusion in combination with bortezomib for multiple myeloma.

Table 7: Frequency of Treatment-Emergent Adverse Reactions Reported in ≥10% Patients Treated for Multiple Myeloma With DOXIL Liposomal Infusion in Combination With Bortezomib
Adverse Reaction | DOXIL Liposomal Infusion + bortezomib (n=318) |  | Bortezomib (n=318)
 | Any (%) | Grade 3–4 | Any (%) | Grade 3–4
Blood and lymphatic system disorders
Neutropenia | 36 | 32 | 22 | 16
Thrombocytopenia | 33 | 24 | 28 | 17
Anemia | 25 | 9 | 21 | 9
General disorders and administration site conditions
Fatigue | 36 | 7 | 28 | 3
Pyrexia | 31 | 1 | 22 | 1
Asthenia | 22 | 6 | 18 | 4
Gastrointestinal disorders
Nausea | 48 | 3 | 40 | 1
Diarrhea | 46 | 7 | 39 | 5
Vomiting | 32 | 4 | 22 | 1
Constipation | 31 | 1 | 31 | 1
Mucositis/Stomatitis | 20 | 2 | 5 | <1
Abdominal pain | 11 | 1 | 8 | 1
Infections and infestations
Herpes zoster | 11 | 2 | 9 | 2
Herpes simplex | 10 | 0 | 6 | 1
Investigations
Weight decreased | 12 | 0 | 4 | 0
Metabolism and Nutritional disorders
Anorexia | 19 | 2 | 14 | <1
Nervous system disorders
Peripheral Neuropathy [Peripheral neuropathy includes the following adverse reactions: peripheral sensory neuropathy, neuropathy peripheral, polyneuropathy, peripheral motor neuropathy, and neuropathy NOS.] | 42 | 7 | 45 | 11
Neuralgia | 17 | 3 | 20 | 4
Paresthesia/dysesthesia | 13 | <1 | 10 | 0
Respiratory, thoracic and mediastinal disorders
Cough | 18 | 0 | 12 | 0
Skin and subcutaneous tissue disorders
Rash [Rash includes the following adverse reactions: rash, rash erythematous, rash macular, rash maculo-papular, rash pruritic, exfoliative rash, and rash generalized.] | 22 | 1 | 18 | 1
Hand-foot syndrome | 19 | 6 | <1 | 0

6.2 Postmarketing Experience

The following additional adverse reactions have been identified during postapproval use of DOXIL liposomal infusion. Because these reactions are reported voluntarily from a population of uncertain size, it is not always possible to reliably estimate their frequency or establish a causal relationship to drug exposure.

Musculoskeletal and Connective Tissue Disorders: muscle spasms

Respiratory, Thoracic and Mediastinal Disorders: pulmonary embolism (in some cases fatal)

Hematologic Disorders: Secondary acute myelogenous leukemia

Skin and Subcutaneous Tissue Disorders: erythema multiforme, Stevens‑Johnson syndrome, toxic epidermal necrolysis, lichenoid keratosis

Secondary Oral Neoplasms: [see Warnings and Precautions (5.4)].

Renal and urinary disorders: Cases of Renal-limited thrombotic microangiopathy have been reported in patients with high cumulative exposure to DOXIL liposomal infusion.

7 DRUG INTERACTIONS

No formal drug interaction studies have been conducted with DOXIL liposomal infusion.

8 USE IN SPECIFIC POPULATIONS

8.1 Pregnancy

Risk Summary

Based on findings in animals and its mechanism of action, DOXIL liposomal infusion can cause fetal harm when administered to a pregnant woman; avoid the use of DOXIL liposomal infusion during the 1st trimester. In animal reproduction studies, DOXIL liposomal infusion was embryotoxic in rats and abortifacient in rabbits following intravenous administration during organogenesis at doses approximately 0.12 times the recommended clinical dose (see Data). Available human data do not establish the presence or absence of major birth defects and miscarriage related to the use of doxorubicin hydrochloride during the 2nd and 3rd trimesters. Advise pregnant women of the potential risk to a fetus.

The background risk of major birth defects and miscarriage for the indicated populations are unknown. However, the background risk in the U.S. general population of major birth defects is 2–4% and of miscarriage is 15–20% of clinically recognized pregnancies.

Data

Animal Data

DOXIL liposomal infusion was embryotoxic at doses of 1 mg/kg/day in rats and was embryotoxic and abortifacient at 0.5 mg/kg/day in rabbits (both doses are about 0.12 times the recommended dose of 50 mg/m^2 human dose on a mg/m^2 basis). Embryotoxicity was characterized by increased embryo-fetal deaths and reduced live litter sizes.

8.2 Lactation

Risk Summary

It is not known whether DOXIL liposomal infusion is present in human milk. Because many drugs, including anthracyclines, are excreted in human milk and because of the potential for serious adverse reactions in breastfed infants from DOXIL liposomal infusion, discontinue breastfeeding during treatment with DOXIL liposomal infusion.

8.3 Females and Males of Reproductive Potential

Pregnancy Testing

Verify the pregnancy status of females of reproductive potential prior to initiating DOXIL liposomal infusion.

Contraception

Females

DOXIL liposomal infusion can cause fetal harm when administered to a pregnant woman [see Use in Specific Populations (8.1)]. Advise females of reproductive potential to use effective contraception during and for 6 months after treatment with DOXIL liposomal infusion.

Males

DOXIL liposomal infusion may damage spermatozoa and testicular tissue, resulting in possible genetic fetal abnormalities. Males with female sexual partners of reproductive potential should use effective contraception during and for 6 months after treatment with DOXIL liposomal infusion [see Non-clinical Toxicology (13.1)].

Infertility

Females

In females of reproductive potential, DOXIL liposomal infusion may cause infertility and result in amenorrhea. Premature menopause can occur with doxorubicin hydrochloride. Recovery of menses and ovulation is related to age at treatment.

Males

DOXIL liposomal infusion may result in oligospermia, azoospermia, and permanent loss of fertility. Sperm counts have been reported to return to normal levels in some men. This may occur several years after the end of therapy [see Non-clinical Toxicology (13.1)].

8.4 Pediatric Use

The safety and effectiveness of DOXIL liposomal infusion in pediatric patients have not been established.

8.5 Geriatric Use

Clinical studies of DOXIL liposomal infusion conducted in patients with either epithelial ovarian cancer (Trial 4) or with AIDS-related Kaposi’s sarcoma (Trial 5) did not contain sufficient numbers of patients aged 65 and over to determine whether they respond differently from younger subjects.

In Trial 6, of 318 patients treated with DOXIL liposomal infusion in combination with bortezomib for multiple myeloma, 37% were 65 years of age or older and 8% were 75 years of age or older. No overall differences in safety or efficacy were observed between these patients and younger patients.

8.6 Hepatic Impairment

The pharmacokinetics of DOXIL liposomal infusion has not been adequately evaluated in patients with hepatic impairment. Doxorubicin is eliminated in large part by the liver. Reduce DOXIL liposomal infusion for serum bilirubin of 1.2 mg/dL or higher.

10 OVERDOSAGE

Acute overdosage with doxorubicin hydrochloride causes increased risk of severe mucositis, leukopenia, and thrombocytopenia.

11 DESCRIPTION

The active ingredient in DOXIL liposomal infusion is doxorubicin hydrochloride, an anthracycline topoisomerase inhibitor, that is encapsulated in STEALTH liposomes for intravenous use.

The chemical name of doxorubicin hydrochloride is (8S,10S)-10-[(3-amino-2,3,6‑trideoxy-α-L-lyxo-hexopyranosyl)oxy]-8-glycolyl-7,8,9,10-tetrahydro-6,8,11‑trihydroxy-1-methoxy-5,12-naphthacenedione hydrochloride. The molecular formula is C27-H29 -NO11•HCl and the molecular weight is 579.99.

The structural formula is:

DOXIL liposomal infusion is a sterile, translucent, red liposomal dispersion. Each single-dose vial contains 20 mg or 50 mg doxorubicin hydrochloride at a concentration of 2 mg/mL (equivalent to 1.87 mg/mL of doxorubicin). The STEALTH liposome carriers are composed of cholesterol, 3.19 mg/mL; fully hydrogenated soy phosphatidylcholine (HSPC), 9.58 mg/mL; and N-(carbonyl-methoxypolyethylene glycol 2000)-1,2-distearoyl-sn-glycero-3-phosphoethanolamine sodium salt (MPEG-DSPE), 3.19 mg/mL. Each mL also contains ammonium sulfate, approximately 0.6 mg; histidine, 1.55 mg as a buffer; hydrochloric acid and/or sodium hydroxide may have been added for pH adjustment (6.0 to 7.0); and sucrose, 94 mg to maintain isotonicity. Greater than 90% of the drug is encapsulated in the STEALTH liposomes.

MPEG-DSPE has the following structural formula:

HSPC has the following structural formula:

Representation of a STEALTH liposome:

12 CLINICAL PHARMACOLOGY

12.1 Mechanism of Action

The active ingredient of DOXIL liposomal infusion is doxorubicin hydrochloride. The mechanism of action of doxorubicin hydrochloride is thought to be related to its ability to bind DNA and inhibit nucleic acid synthesis. Cell structure studies have demonstrated rapid cell penetration and perinuclear chromatin binding, rapid inhibition of mitotic activity and nucleic acid synthesis, and induction of mutagenesis and chromosomal aberrations.

12.3 Pharmacokinetics

The pharmacokinetic parameters for total doxorubicin following a single dose of DOXIL infused over 30 minutes are presented in Table 8.

Table 8: Pharmacokinetic Parameters of Total Doxorubicin from DOXIL Liposomal Infusion in Patients With AIDS-Related Kaposi’s Sarcoma
 | Dose
Parameter (units) | 10 mg/m^2 | 20 mg/m^2
Peak Plasma Concentration (µg/mL) | 4.12 ± 0.215 | 8.34 ± 0.49
Plasma Clearance (L/h/m^2) | 0.056 ± 0.01 | 0.041 ± 0.004
Steady State Volume of Distribution (L/m^2) | 2.83 ± 0.145 | 2.72 ± 0.120
AUC (µg/mL∙h) | 277 ± 32.9 | 590 ± 58.7
First Phase (λ1) Half-Life (h) | 4.7 ± 1.1 | 5.2 ± 1.4
Second Phase (λ1) Half-Life (h) | 52.3 ± 5.6 | 55.0 ± 4.8
N=23
Mean ± Standard Error

DOXIL liposomal infusion displayed linear pharmacokinetics over the range of 10 to 20 mg/m^2. Relative to DOXIL liposomal infusion doses at or below 20 mg/m^2, the pharmacokinetics of total doxorubicin following a 50 mg/m^2 DOXIL liposomal infusion dose are nonlinear. At this dose, the elimination half-life of DOXIL liposomal infusion is longer and the clearance lower compared to a 20 mg/m^2 dose.

Distribution

Direct measurement of liposomal doxorubicin shows that at least 90% of the drug (the assay used cannot quantify less than 5–10% free doxorubicin) remains liposome-encapsulated during circulation.

In contrast to doxorubicin, which displays a large volume of distribution (range 700 to 1100 L/m^2), the small steady state volume of distribution of liposomal doxorubicin suggests that DOXIL liposomal infusion is largely confined to vascular fluid. Doxorubicin becomes available after the liposomes are extravasated. Plasma protein binding of DOXIL liposomal infusion has not been determined; the plasma protein binding of doxorubicin is approximately 70%.

Metabolism

Doxorubicinol, the major metabolite of doxorubicin, was detected at concentrations of 0.8 to 26.2 ng/mL in the plasma of patients who received 10 or 20 mg/m^2 DOXIL liposomal infusion.

Elimination

The plasma clearance of total doxorubicin from DOXIL liposomal infusion was 0.041 L/h/m^2 at a dose of 20 mg/m^2. Following administration of doxorubicin hydrochloride, the plasma clearance of doxorubicin is 24 to 35 L/h/m^2.

13 NON-CLINICAL TOXICOLOGY

13.1 Carcinogenesis, Mutagenesis, and Impairment of Fertility

Mutagenicity or carcinogenicity studies have not been conducted with DOXIL liposomal infusion, however doxorubicin was shown to be mutagenic in the in vitro Ames assay, and clastogenic in multiple in vitro assays (CHO cell, V79 hamster cell, human lymphoblast, and SCE assays) and the in vivo mouse micronucleus assay. The possible adverse effects on fertility in animals have not been adequately evaluated. DOXIL liposomal infusion resulted in mild to moderate ovarian and testicular atrophy in mice after administration of a single dose of 36 mg/kg (about 2 times the 50 mg/m^2 human dose on a mg/m^2 basis). Decreased testicular weights and hypospermia were observed in rats after repeat doses ≥ 0.25 mg/kg/day (about 0.03 times the 50 mg/m^2 human dose on a mg/m^2 basis), and diffuse degeneration of the seminiferous tubules and a marked decrease in spermatogenesis were observed in dogs after repeat doses of 1 mg/kg/day (about 0.4 times the 50 mg/m^2 human dose on a mg/m^2 basis).

14 CLINICAL STUDIES

14.1 Ovarian Cancer

DOXIL liposomal infusion was studied in three open-label, single-arm, clinical studies of 176 patients with metastatic ovarian cancer (Trials 1, 2, and 3). One hundred forty-five of these patients were refractory to both paclitaxel- and platinum-based chemotherapy regimens, defined as disease progression while on treatment or relapse within 6 months of completing treatment. Patients received DOXIL liposomal infusion at 50 mg/m^2 every 3 or 4 weeks for 3–6+ cycles in the absence of dose-limiting toxicity or disease progression.

The median age at diagnosis ranged from 52 to 64 years in the 3 studies, and the range was 22 to 85. Most patients had International Federation of Obstetricians and Gynecologists (FIGO) stage III or IV disease (ranging from 83% to 93%). Approximately one third of the patients had three or more prior lines of therapy (ranging from 22% to 33%).

The primary outcome measure was confirmed response rate based on Southwestern Oncology Group (SWOG) criteria for patients refractory to both paclitaxel- and a platinum-containing regimen. Secondary efficacy parameters were time to response, duration of response, and time to progression.

The response rates for the individual single arm trials are given in Table 9 below.

Table 9: Response Rates in Patients With Refractory Ovarian Cancer From Single Arm Ovarian Cancer Trials
 | Trial 1 (U.S.) N=27 | Trial 2 (U.S.) N=82 | Trial 3 (non-U.S.) N=36
Response Rate | 22.2% | 17.1% | 0%
95% Confidence Interval | 8.6% – 42.3% | 9.7% – 27.0% | 0.0% – 9.7%

In a pooled analysis of Trials 1–3, the response rate for all patients refractory to paclitaxel and platinum agents was 13.8% (95% CI 8.1% to 19.3%). The median time to progression was 15.9 weeks, the median time to response was 17.6 weeks, and the duration of response was 39.4 weeks.

In Trial 4, a randomized, multicenter, open-label, trial in 474 patients with epithelial ovarian cancer after platinum-based chemotherapy, patients were randomized to receive either DOXIL liposomal infusion 50 mg/m^2 every 4 weeks (n=239) or topotecan 1.5 mg/m^2 daily for 5 consecutive days every 3 weeks (n=235). Patients were stratified according to platinum sensitivity (response to initial platinum-based therapy and a progression-free interval of greater than 6 months off treatment) and the presence of bulky disease (tumor mass greater than 5 cm in size). The primary outcome measure was time to progression (TTP). Other endpoints included overall survival and objective response rate.

Of the 474 patients, the median age at diagnosis was 60 years (range 25 to 87), 90% were FIGO stage III and IV; 46% were platinum sensitive; and 45% had bulky disease.

There was no statistically significant difference in TTP between the two arms. Results are provided in Table 10.

Table 10: Results of Efficacy Analyses [Analysis based on investigators' strata for protocol defined ITT population.]
 | Protocol Defined ITT Population
 | DOXIL Liposomal Infusion (n=239) | Topotecan (n=235)
TTP (Protocol Specified Primary Endpoint)
Median (Months) [Kaplan-Meier estimates.] | 4.1 | 4.2
p-value [p-value is based on the stratified log-rank test.] | 0.62
Hazard Ratio [Hazard ratio is based on Cox proportional-hazard model with the treatment as single independent variable. A hazard ratio less than 1 indicates an advantage for DOXIL liposomal infusion.] | 0.96
95% CI for Hazard Ratio | (0.76, 1.20)
Overall Survival
Median (Months) | 14.4 | 13.7
p-value [p-value not adjusted for multiple comparisons.] | 0.05
Hazard Ratio | 0.82
95% CI for Hazard Ratio | (0.68, 1.00)
Response Rate
Overall Response n (%) | 47 (19.7) | 40 (17.0)
Complete Response n (%) | 9 (3.8) | 11 (4.7)
Partial Response n (%) | 38 (15.9) | 29 (12.3)
Median Duration of Response (Months) | 6.9 | 5.9

14.2 AIDS-Related Kaposi’s Sarcoma

DOXIL liposomal infusion was studied in an open-label, single-arm, multicenter study at a dose of 20 mg/m^2 every 3 weeks, until disease progression or unacceptable toxicity (Trial 5).

Data is described for a cohort of 77 patients retrospectively identified as having disease progression on prior systemic combination chemotherapy (at least two cycles of a regimen containing at least two of three treatments: bleomycin, vincristine or vinblastine, or doxorubicin) or as being intolerant to such therapy. Forty-nine of the 77 (64%) patients had received prior doxorubicin hydrochloride.

The median time on study was 5.1 months (range 1 day to 15 months). The median cumulative dose of DOXIL liposomal infusion was 154 mg/m^2 (range 20 to 620 mg/m^2). Among the 77 patients, mean age was 38 years (range 24 to 54); 87% were Caucasian, 5% Hispanic, 4% Black, and 4% Asian/Other/Unknown; median CD4 count was 10 cells/mm^3; ACTG staging criteria were 78% poor risk for tumor burden, 96% poor risk for immune system, and 58% poor risk for systemic illness at baseline; and mean Karnofsky status score was 74%. All patients had cutaneous or subcutaneous lesions, 40% also had oral lesions, 26% pulmonary lesions, and 14% had lesions of the stomach/intestine.

Two analyses of tumor response were used: one based on investigator assessment of changes in lesions based on modified ACTG criteria (partial response defined as no new lesions, sites of disease, or worsening edema; flattening of ≥50% of previously raised lesions or area of indicator lesions decreasing by ≥50%; and response lasting at least 21 days with no prior progression), and one based on changes in up to five prospectively identified representative indicator lesions (partial response defined as flattening of ≥50% of previously raised indicator lesions, or >50% decrease in the area of indicator lesions and lasting at least 21 days with no prior progression).

Of the 77 patients, 34 were evaluable for investigator assessment and 42 were evaluable for indicator lesion assessment; analyses of tumor responses are shown in Table 11.

Table 11: Response in Patients with Refractory [Patients with disease that progressed on prior combination chemotherapy or who were intolerant to such therapy.] AIDS-Related Kaposi’s Sarcoma
Investigator Assessment | All Evaluable Patients (n=34) | Evaluable Patients Who Received Prior Doxorubicin (n=20)
Response [There were no complete responses in this population.]
Partial (PR) | 27% | 30%
Stable | 29% | 40%
Progression | 44% | 30%
Duration of PR (Days)
Median | 73 | 89
Range | 42+ – 210+ | 42+ – 210+
Time to PR (Days)
Median | 43 | 53
Range | 15 – 133 | 15 – 109
Indicator Lesion Assessment | All Evaluable Patients (n=42) | Evaluable Patients Who Received Prior Doxorubicin (n=23)
Response
Partial (PR) | 48% | 52%
Stable | 26% | 30%
Progression | 26% | 17%
Duration of PR (Days)
Median | 71 | 79
Range | 22+ – 210+ | 35 – 210+
Time to PR (Days)
Median | 22 | 48
Range | 15 – 109 | 15 – 109

Retrospective efficacy analyses were performed in two trials that had subsets of patients who received single-agent DOXIL liposomal infusion and who were on stable antiretroviral therapy for at least 60 days prior to enrollment and until a response was demonstrated. In one trial, 7 of 17 (40%) patients had a durable response (median duration not reached but was longer than 11.6 months). In the second trial, 4 of 11 patients (40%) on a stable antiretroviral therapy demonstrated durable responses.

14.3 Multiple Myeloma

The efficacy of DOXIL liposomal infusion in combination with bortezomib was evaluated in Trial 6, a randomized, open-label, international, multicenter study in 646 patients who had not previously received bortezomib and whose disease progressed during or after at least one prior therapy. Patients were randomized (1:1) to receive either DOXIL liposomal infusion (30 mg/m^2) administered IV on day 4 following bortezomib (1.3 mg/m^2 IV on days 1, 4, 8 and 11) or bortezomib alone every 3 weeks for up to 8 cycles or until disease progression or unacceptable toxicity. Patients who maintained a response were allowed to receive further treatment. The median number of cycles in each treatment arm was 5 (range 1–18).

The baseline demographics and clinical characteristics of the patients with multiple myeloma were similar between treatment arms (Table 12).

Table 12: Summary of Baseline Patient and Disease Characteristics
Patient Characteristics | DOXIL Liposomal Infusion + bortezomib n=324 | bortezomib n=322
Median age in years (range) | 61 (28, 85) | 62 (34, 88)
% Male/female | 58 / 42 | 54 / 46
% Caucasian/Black/other | 90 / 6 / 4 | 94 / 4 / 2
Disease Characteristics
% with IgG/IgA/Light chain | 57 / 27 / 12 | 62 / 24 / 11
% β2-microglobulin group
≤2.5 mg/L | 14 | 14
>2.5 mg/L and ≤5.5 mg/L | 56 | 55
>5.5 mg/L | 30 | 31
Serum M-protein (g/dL): Median (Range) | 2.5 (0–10.0) | 2.7 (0–10.0)
Urine M-protein (mg/24 hours): Median (Range) | 107 (0–24883) | 66 (0–39657)
Median Months Since Diagnosis | 35.2 | 37.5
% Prior Therapy
One | 34 | 34
More than one | 66 | 66
Prior Systemic Therapies for Multiple Myeloma
Corticosteroid (%) | 99 | >99
Anthracyclines | 68 | 67
Alkylating agent (%) | 92 | 90
Thalidomide/lenalidomide (%) | 40 | 43
Stem cell transplantation (%) | 57 | 54

The primary outcome measure was time to progression (TTP). TTP was defined as the time from randomization to the first occurrence of progressive disease or death due to progressive disease. The combination arm demonstrated significant improvement in TTP. As the prespecified primary objective was achieved at the interim analysis, patients in the bortezomib monotherapy group were then allowed to receive the DOXIL liposomal infusion + bortezomib combination. Efficacy results are as shown in Table 13 and Figure 1.

Table 13: Efficacy of DOXIL Liposomal Infusion in Combination With Bortezomib in the Treatment of Patients With Multiple Myeloma
Endpoint | DOXIL Liposomal Infusion + bortezomib n=324 | Bortezomib n=322
Time to Progression [Kaplan Meier estimate.]
Progression or death due to progression (n) | 99 | 150
Censored (n) | 225 | 172
Median in days (months) | 282 (9.3) | 197 (6.5)
95% CI | 250; 338 | 170; 217
Hazard ratio [Hazard ratio based on stratified Cox proportional hazards regression. A hazard ratio < 1 indicates an advantage for DOXIL liposomal infusion +bortezomib.] | 0.55
(95% CI) | (0.43, 0.71)
p-value [Stratified log-rank test.] | <0.001
Response (n) [RR as per EBMT criteria.] | 303 | 310
% Complete Response (CR) | 5 | 3
% Partial Response (PR) | 43 | 40
% CR + PR | 48 | 43
p-value [Cochran-Mantel-Haenszel test adjusted for the stratification factors.] | 0.25
Median Duration of Response (months) | 10.2 | 7.0
(95% CI) | (10.2; 12.9) | (5.9; 8.3)

Figure 1 - Time to Progression Kaplan-Meier Curve

At the final analysis of survival, 78% of subjects in the DOXIL liposomal infusion and bortezomib combination therapy group and 80% of subjects in the bortezomib monotherapy group had died after a median follow up of 8.6 years. The median survival was 33 months in the DOXIL liposomal infusion and bortezomib combination therapy group and 31 months in the bortezomib monotherapy group. There was no difference observed in overall survival at the final analysis [HR for DOXIL liposomal infusion + bortezomib vs. bortezomib = 0.96 (95% CI 0.80, 1.14)].

Seventy-eight percent of subjects in the DOXIL liposomal infusion and bortezomib combination therapy group and 80% of subjects in the bortezomib monotherapy group had received subsequent therapy.

15 REFERENCES

1. “Hazardous Drugs”, OSHA, http://www.osha.gov/SLTC/hazardousdrugs/index.html

16 HOW SUPPLIED/STORAGE AND HANDLING

DOXIL (doxorubicin hydrochloride liposome injection) is a sterile, translucent, red liposomal dispersion in 10-mL or 30-mL glass, single-dose vials.

The following individually cartoned vials are available:

Table 14
vial concentration |  | vial size | NDC #s
20 mg/10 mL; (2 mg/ mL) |  | 10-mL | 0338-9667-01
50 mg/25 mL; (2 mg/mL) |  | 30-mL | 0338-9665-01

STORAGE AND HANDLING

Refrigerate unopened vials of DOXIL (doxorubicin hydrochloride liposome injection) at 2°C- 8°C (36°F- 46°F). Do not freeze. Discard unused portion.

DOXIL liposomal infusion is a cytotoxic drug. Follow applicable special handling and disposal procedures.^1

17 PATIENT COUNSELING INFORMATION

Cardiomyopathy

Advise patients to contact their healthcare provider if they develop symptoms of heart failure [see Warnings and Precautions (5.1)].

Infusion-Related Reactions

Advise patients about the symptoms of infusion related reactions and to seek immediate medical attention if they develop any of these symptoms [see Warnings and Precautions (5.2)].

Myelosuppression

Advise patients to contact their healthcare provider for a new onset fever or symptoms of infection.

Hand-Foot Syndrome

Advise patients to notify their healthcare provider if they experience tingling or burning, redness, flaking, bothersome swelling, small blisters, or small sores on the palms of their hands or soles of their feet (symptoms of Hand-Foot Syndrome) [see Warnings and Precautions (5.3)].

Stomatitis

Advise patients to notify their healthcare provider if they develop painful redness, swelling, or sores in the mouth (symptoms of stomatitis).

Embryo-Fetal Toxicity

Advise females of reproductive potential of the potential risk to a fetus and to inform their healthcare provider with a known or suspected pregnancy [see Warnings and Precautions (5.5) and Use in Specific Populations (8.1)].

Advise females and males of reproductive potential to use effective contraception during and for 6 months following treatment with DOXIL liposomal infusion [see Use in Specific Populations (8.3)].

Lactation

Advise females not to breastfeed during treatment with DOXIL liposomal infusion [see Use in Specific Populations (8.2)].

Infertility

Advise females and males of reproductive potential that DOXIL liposomal infusion may cause temporary or permanent infertility [see Use in Specific Populations (8.3)].

Discoloration of Urine and Body Fluids

Inform patients that following DOXIL liposomal infusion administration, a reddish-orange color to the urine and other body fluids may be observed. This nontoxic reaction is due to the color of the product and will dissipate as the drug is eliminated from the body.

Manufactured for:
Baxter Healthcare Corporation
Deerfield, IL 60015 USA
Made in Germany

Baxter, Doxil, and Stealth are trademarks of Baxter International Inc. or its subsidiaries.

HA-30-02-689

PRINCIPAL DISPLAY PANEL – 20 mg

NDC 0338-9667-01
Rx only

DOXIL
(DOXOrubicin Hydrochloride
liposome injection)

20 mg in 10 mL (2 mg/mL)

Single-Dose Vial. Discard unused portion.

LIPOSOMAL FORMULATION - DO NOT
SUBSTITUTE FOR DOXORUBICIN Hydrochloride

FOR INTRAVENOUS INFUSION ONLY
Cytotoxic
Refrigerate, 2°-8°C (36°-46°F). Do Not Freeze.

See package insert for dosage information.

Baxter Healthcare Corporation Deerfield, IL 60015

Carton Label

NDC 0338-9667-01
DOXIL
(DOXOrubicin
Hydrochloride
liposome injection)

20 mg in 10 mL
(2 mg/mL)

Single-Dose Vial. Discard unused portion.

LIPOSOMAL FORMULATION -
DO NOT SUBSTITUTE
FOR DOXORUBICIN Hydrochloride

FOR INTRAVENOUS
INFUSION ONLY
AFTER DILUTION.

Refrigerate, 2°-8°C
(36°-46°F). Do Not Freeze.
Cytotoxic

Rx only

Baxter

PACKAGE/LABEL PRINCIPAL DISPLAY PANEL – 50 mg

NDC 0338-9665-01
Rx only

DOXIL
(DOXOrubicin Hydrochloride liposome injection)

50 mg in 25 mL (2 mg/mL)

Single-Dose Vial. Discard unused portion.

LIPOSOMAL FORMULATION - DO NOT
SUBSTITUTE FOR DOXORUBICIN Hydrochloride

FOR INTRAVENOUS INFUSION ONLY

Cytotoxic

Refrigerate, 2°-8°C (36°-46°F). Do Not Freeze.

See package insert for dosage information.

Baxter Healthcare Corporation Deerfield, IL 60015

Carton Label

NDC 0338-9665-01

DOXIL
(DOXOrubicin
Hydrochloride
liposome injection)

50 mg in 25 mL
(2 mg/mL)

Single-Dose Vial. Discard unused portion.

LIPOSOMAL FORMULATION -
DO NOT SUBSTITUTE
FOR DOXORUBICIN Hydrochloride

FOR INTRAVENOUS
INFUSION ONLY
AFTER DILUTION.

Refrigerate, 2°-8°C
(36°-46°F). Do Not Freeze.
Cytotoxic

Rx only

Baxter